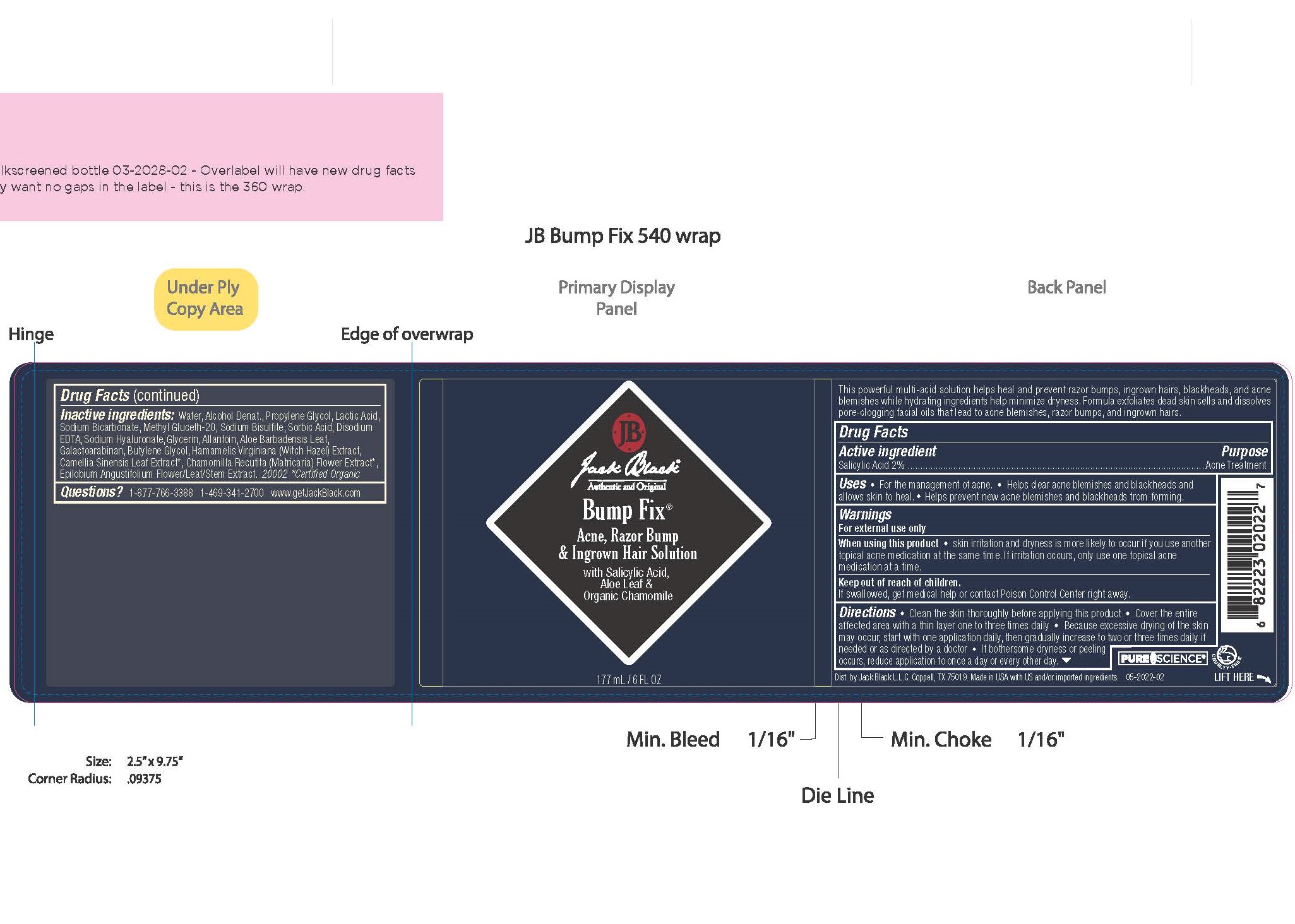 DRUG LABEL: Jack Black Bump Fix
NDC: 66738-022 | Form: LIQUID
Manufacturer: Jack Black, L.L.C.
Category: otc | Type: HUMAN OTC DRUG LABEL
Date: 20231107

ACTIVE INGREDIENTS: SALICYLIC ACID 20 g/1000 g
INACTIVE INGREDIENTS: WATER; ALCOHOL; PROPYLENE GLYCOL; LACTIC ACID; SODIUM BICARBONATE; METHYL GLUCETH-20; SODIUM BISULFITE; SORBIC ACID; EDETATE DISODIUM; HYALURONIC ACID; GLYCERIN; ALLANTOIN; ALOE VERA LEAF; GALACTOARABINAN; BUTYLENE GLYCOL; HAMAMELIS VIRGINIANA TOP; GREEN TEA LEAF; CHAMOMILE; EPILOBIUM ANGUSTIFOLIUM FLOWERING TOP

Jack Black Bump Fix

Warnings

For external use only. When using this product skin irritation and dryness is more likely to occur if you use another topical acne medication at the same time. If irritation occurs, only use one topical acne medication at a time. If swallowed, get medical help or contact Poison Control Center right away.

Keep out of reach of children

Uses

For the management of acne. Helps clear acne blemishes and blackheads and allows skin to heal. Helps prevent new acne blemishes and blackheads form forming.

Uses

For the management of acne. Helps clear acne blemishes and blackheads and allows skin to heal. Helps prevent new acne blemishes and blackheads form forming.

Directions

Clean the skin thoroughly before applying this product. Cover the entire affected area with a think layer one to three times daily. Because excesssive drying of the skin may occur, start with one application daily, then gradually increase to two or three times daily if needed or as directed by a doctor. If bothersome dryness orpeeling occurs, reduce application to once a day or every other day.

Active Ingredient

Salicylic Acid 2%

Inactive Ingredients

water, alcohol denatured, propylene glycol, lactic acid, sodium bicarbonate, methyl glyceth-20, sodium bisulfite, sorbic acid, disodium EDTA, sodium hyaluronate, glycerin, allantoin, aloe barbadensis leaf, galactoarabinan, butylene glycol, hamamelis virginiana (witch hazel) extract, camellia sinensis leaf extract, chamomilla recutita(matricaria) flower extract, epilobium angustifolium flower/leaf/stem extract

Questions

Questions? 1-877-766-3388

1-469-341-2700

www.getjackblack.com